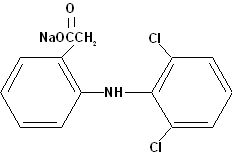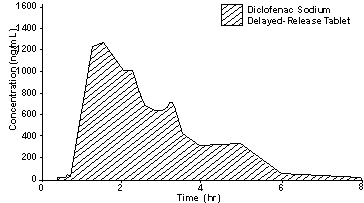 DRUG LABEL: Unknown
Manufacturer: Boehringer Ingelheim Roxane Laboratories
Category: prescription | Type: Human prescription drug label
Date: 20060830

Diclofenac Sodium Delayed-Release Tablets USP
25 mg, 50 mg, 75 mg

Rx only

DESCRIPTION

Diclofenac sodium, is a benzene-acetic acid derivative, designated chemically as 2-[(2,6-dichlorophenyl)amino] benzeneacetic acid, monosodium salt. The structural formula is:

C14H10Cl2NNaO2 M.W. 318.14

Diclofenac sodium is a faintly yellowish white to light beige, virtually odorless, slightly hygroscopic crystalline powder. It is freely soluble in methanol, soluble in ethanol, sparingly soluble in water and practically insoluble in chloroform and in dilute acid. The n-octanol/water partition coefficient is 13.4 at pH 7.4 and 1545 at pH 5.2. Diclofenac sodium has a dissociation constant (pKa) of 4.0 ± 0.2 at 25°C in water.

Each enteric-coated tablet, for oral administration, contains 25 mg, 50 mg, or 75 mg of diclofenac sodium. In addition, each tablet contains the following inactive ingredients: colloidal silicon dioxide, croscarmellose sodium, enteric-coating (black iron oxide, FD&C Blue No. 2, FD&C Red No. 40, FD&C Yellow No. 6, methacrylic acid copolymer, methylparaben, n-butyl alcohol, polysorbate 80, potassium sorbate, propylene glycol, propylparaben, sodium citrate, sodium lauryl sulfate, talc, titanium dioxide, triethyl citrate, and xanthan gum), lactose monohydrate, magnesium stearate, microcrystalline cellulose, pregelatinized starch, and stearic acid.

CLINICAL PHARMACOLOGY

Pharmacodynamics

Diclofenac is a nonsteroidal anti-inflammatory drug (NSAID). In pharmacologic studies, diclofenac has shown anti-inflammatory, analgesic, and antipyretic activity. As with other NSAIDs, its mode of action is not known; its ability to inhibit prostaglandin synthesis, however, may be involved in its anti-inflammatory activity.

Pharmacokinetics

Diclofenac sodium delayed-release tablets are in a pharmaceutic formulation that resists dissolution in the low pH of gastric fluid but allows a rapid release of drug in the higher pH-environment in the duodenum. Its pattern of drug release and absorption is illustrated below:

± 1 SD plasma diclofenac concentrations after a single dose of a 50 mg diclofenac sodium delayed-release tablet (N=38)

Absorption

When diclofenac sodium delayed-release tablets are administered orally after fasting, diclofenac is completely absorbed from the gastrointestinal tract. Of this, only 50% of the absorbed dose of diclofenac from diclofenac sodium is systemically available, due to first-pass metabolism. Peak plasma levels are achieved in 2 hours in fasting normal volunteers, with a range from 1 to 4 hours. The area-under-the plasma-concentration curve (AUC) is dose-proportional within the range of 25 mg to 150 mg. Peak plasma levels are less than dose-proportional and are approximately 1.0, 1.5, and 2 µg/mL for 25 mg, 50 mg and 75 mg doses, respectively. It should be noted that the administration of several individual diclofenac sodium tablets may not yield equivalent results in peak concentration as the administration of one tablet of a higher strength. This is probably due to the staggered gastric emptying of tablets into the duodenum. After repeated oral administration of diclofenac sodium 50 mg b.i.d., diclofenac did not accumulate in plasma.

When diclofenac sodium is taken with food, there is usually a delay in the onset of absorption of 1 to 4.5 hours, with delays as long as 10 hours in some patients, and a reduction in peak plasma levels of approximately 40%. The extent of absorption of diclofenac, however, is not significantly affected by food intake.

Distribution

Plasma concentrations of diclofenac decline from peak levels in a biexponential fashion, with the terminal phase having a half-life of approximately 2 hours. Clearance and volume of distribution are about 350 mL/min and 550 mL/kg, respectively. More than 99% of diclofenac is reversibly bound to human plasma albumin.

A 4-week study, comparing plasma level profiles of diclofenac (diclofenac sodium 50 mg b.i.d.) in younger (26 to 46 years) versus older (66 to 81 years) adults, did not show differences between age groups (10 patients per age group).

As with other NSAIDs, diclofenac diffuses into and out of the synovial fluid. Diffusion into the joint occurs when plasma levels are higher than those in the synovial fluid, after which the process reverses and synovial fluid levels are higher than plasma levels. It is not known whether diffusion into the joint plays a role in the effectiveness of diclofenac.

Metabolism and Elimination

Diclofenac is eliminated through metabolism and subsequent urinary and biliary excretion of the glucuronide and the sulfate conjugates of the metabolites. Approximately 65% of the dose is excreted in the urine, and approximately 35% in the bile.

Conjugates of unchanged diclofenac account for 5 to 10% of the dose excreted in the urine and for less than 5% excreted in the bile. Little or no unchanged unconjugated drug is excreted. Conjugates of the principal metabolite account for 20 to 30% of the dose excreted in the urine and for 10 to 20% of the dose excreted in the bile. Conjugates of three other metabolites together account for 10 to 20% of the dose excreted in the urine and for small amounts excreted in the bile. The elimination half-life values for these metabolites are shorter than those for the parent drug. Urinary excretion of an additional metabolite (half-life 80 hours) accounts for only 1.4% of the oral dose. The degree of accumulation of diclofenac metabolites is unknown. Some of the metabolites may have activity.

Patients with Renal and/or Hepatic Impairment

To date, no differences in the pharmacokinetics of diclofenac have been detected in studies of patients with renal (50 mg intravenously) or hepatic impairment (100 mg oral solution). In patients with renal impairment (N=5, creatinine clearance 3 to 42 mL/min), AUC values and elimination rates were comparable to those in healthy subjects. In patients with biopsy-confirmed cirrhosis or chronic active hepatitis (variably elevated transaminases and mildly elevated bilirubins, N=10), diclofenac concentrations and urinary elimination values were comparable to those in healthy subjects.

Clinical Studies

Osteoarthritis:

Diclofenac sodium was evaluated for the management of the signs and symptoms of osteoarthritis of the hip or knee in a total of 633 patients treated for up to 3 months in placebo and active-controlled clinical trials against aspirin (N=449), and naproxen (N=92). Diclofenac sodium was given both in variable (100 to 150 mg/day) and fixed (150 mg/day) dosing schedules on either b.i.d. or t.i.d. dosing regimens. In these trials, diclofenac sodium was found to be comparable to 2400 to 3600 mg/day of aspirin or 500 mg/day of naproxen. Diclofenac was effective when administered as either b.i.d. or t.i.d. dosing regimens.

Rheumatoid Arthritis:

Diclofenac sodium was evaluated for managing the signs and symptoms of rheumatoid arthritis in a total of 468 patients treated for up to 3 months in placebo- and active- controlled clinical trials against aspirin (N=290), and ibuprofen (N = 74). Diclofenac sodium was given in a fixed (150 or 200 mg/day) dosing schedule as either b.i.d. or t.i.d. dosing regimens. Diclofenac sodium was found to be comparable to 3600 to 4800 mg/day of aspirin, and 2400 mg/day of ibuprofen. Diclofenac sodium was used b.i.d. or t.i.d., administering 150 mg/day in most trials, but 50 mg q.i.d. (200 mg/day) was also studied.

Ankylosing Spondylitis:

Diclofenac sodium was evaluated for the management of the signs and symptoms of ankylosing spondylitis in a total of 132 patients in one active controlled clinical trial against indomethacin (N=130). Both diclofenac sodium and indomethacin patients were started on 25 mg t.i.d. and were permitted to increase the dose 25 mg per day each week to a maximum dose of 125 mg/day. Diclofenac sodium 75 to 125 mg/day was found to be comparable to indomethacin 75 to 125 mg/day.

G.I. Blood Loss/Endoscopy Data:

G.I. blood loss and endoscopy studies were performed with diclofenac sodium delayed-release [enteric-coated] tablets that, unlike immediate-release tablets, do not dissolve in the stomach where the endosopic lesions are primarily seen. A repeat-dose endoscopy study, in patients with rheumatoid arthritis or osteoarthritis treated with diclofenac sodium delayed-release tablets 75 mg b.i.d. (N=101), or naproxen (immediate-release tablets) 500 mg b.i.d. (N=103) for three months, resulted in a significantly smaller number of patients with an increase in endoscopy score from baseline and a significantly lower mean endoscopy score after treatment in the diclofenac sodium treated patients. Two repeat-dose endoscopic studies, in normal volunteers, showed that daily doses of diclofenac sodium delayed-release tablets 75 or 100 mg (N=6 and 14, respectively) for 1 week caused fewer gastric lesions, and those that did occur had lower scores than those observed following daily 500 mg doses of naproxen (immediate-release tablets). In healthy subjects, the daily administration of 150 mg of diclofenac sodium (N=8) for 3 weeks resulted in a mean fecal blood loss of less than that observed with 3 g of aspirin daily (N=8). In four repeat-dose studies, mean fecal blood loss with 150 mg of diclofenac was also less than that observed with 750 mg of naproxen (N=8 and 6) or 150 mg of indomethacin (N=8 and 6). The clinical significance of these findings is unknown since there is no evidence available to indicate that diclofenac sodium is less likely than other drugs of its class to cause serious gastrointestinal lesions when used in chronic therapy.

Individualization of Dosage

Diclofenac, like other NSAIDs, shows interindividual differences in both pharmacokinetics and clinical response (pharmacodynamics). Consequently, the recommended strategy for initiating therapy is to use a starting dose likely to be effective for the majority of patients and to adjust dosage thereafter based on observation of diclofenac’s beneficial and adverse effects.

In patients weighing less than 60 kg (132 lbs), or where the severity of the disease, concomitant medication, or other diseases warrant, the maximum recommended total daily dose of diclofenac should be reduced. Experience with other NSAIDs has shown that starting therapy with maximal doses in patients at increased risk due to renal or hepatic disease, low body weight (<60 kg), advanced age, a known ulcer diathesis, or known sensitivity to NSAID effects, is likely to increase frequency of adverse reactions and is not recommended (see PRECAUTIONS).

Osteoarthritis/Rheumatoid Arthritis/Ankylosing Spon-dylitis:

The usual starting dose of diclofenac sodium delayed-release tablets for patients with osteoarthritis, is 100 to 150 mg/day, using a b.i.d. or t.i.d. dosing regimen. In two variable-dose clinical trials in osteoarthritis, of 266 patients started on 100 mg/day, 176 chose to increase the dose to 150 mg/day. Dosages above 150 mg/day have not been studied in patients with osteoarthritis.

The usual starting dose of diclofenac sodium for most patients with rheumatoid arthritis is 150 mg/day, using a b.i.d. or t.i.d. dosing regimen. Patients requiring more relief of pain and inflammation may increase the dose to 200 mg/day. In clinical trials, patients receiving 200 mg/day were less likely to drop form the trial due to lack of efficacy than patients receiving 150 mg/day. Dosages above 225 mg/day are not recommended in patients with rheumatoid arthritis because of increased risk of adverse events.

The recommended dose of diclofenac sodium delayed-release tablets for patients with ankylosing spondylitis is 100 to 125 mg/day, using a q.i.d. dosing regimen (see DOSAGE AND ADMINISTRATION regarding the 125 mg/day dosage regimen). In a variable-dose clinical trial, of 132 patients started on 75 mg/day, 122 chose to increase the dose to 125 mg/day. Dosages above 125 mg/day have not been studied in patients with ankylosing spondylitis.

INDICATIONS AND USAGE

Diclofenac sodium delayed-release tablets are indicated for the acute and chronic treatment of the signs and symptoms of rheumatoid arthritis, osteoarthritis, and ankylosing spondylitis.

CONTRAINDICATIONS

Diclofenac sodium delayed-release tablets are contraindicated in patients with hypersensitivity to the product. Diclofenac should not be given to patients who have experienced asthma, urticaria, or other allergic-type reactions after taking aspirin or other NSAIDs. Severe, rarely fatal, anaphylactic-like reactions to diclofenac have been reported in such patients.

WARNINGS

Gastrointestinal Effects

Peptic ulceration and gastrointestinal bleeding have been reported in patients receiving diclofenac. Physicians and patients should therefore remain alert for ulceration and bleeding in patients treated chronically with diclofenac even in the absence of previous G.I. tract symptoms. It is recommended that patients be maintained on the lowest dose of diclofenac possible consistent with achieving a satisfactory therapeutic response.

Risk of G.I. Ulcerations, Bleeding, and Perforation with NSAID Therapy

Serious gastrointestinal toxicity such as bleeding, ulceration, and perforation can occur at any time, with or without warning symptoms, in patients treated chronically with NSAID therapy. Although minor upper gastrointestinal problems, such as dyspepsia, are common, usually developing early in therapy, physicians should remain alert for ulceration and bleeding in patients treated chronically with NSAIDs even in the absence of previous G.I. tract symptoms. In patients observed in clinical trials of several months to 2 years duration, symptomatic upper G.I. ulcers, gross bleeding, or perforation appear to occur in approximately 1% of patients for 3 to 6 months, and in about 2 to 4% of patients treated for 1 year. Physicians should inform patients about the signs and/or symptoms of serious G.I. toxicity and what steps to take if they occur.

Studies to date have not identified any subset of patients not at risk of developing peptic ulceration and bleeding. Except for a prior history of serious G.I. events and other risk factors known to be associated with peptic ulcer disease, such as alcoholism, smoking, etc., no risk factors (e.g., age, sex) have been associated with increased risk. Elderly or debilitated patients seem to tolerate ulceration or bleeding less well than other individuals and most spontaneous reports of fatal G.I. events are in this population. Studies to date are inconclusive concerning the relative risk of various NSAIDs in causing such reactions. High doses of any NSAID probably carry a greater risk of these reactions, although controlled clinical trials showing this do not exist in most cases. In considering the use of relatively large doses (within the recommended dosage range), sufficient benefit should be anticipated to offset the potential increased risk of G.I. toxicity.

Hepatic Effects

As with other NSAIDs, elevations of one or more liver tests may occur during diclofenac therapy. These laboratory abnormalities may progress, may remain unchanged, or may be transient with continued therapy. Borderline elevations, (i.e., less than 3 times the ULN [=the Upper Limit of the Normal range]), or greater elevations of transaminases occurred in about 15% of diclofenac-treated patients. Of the hepatic enzymes, ALT (SGPT) is the one recommended for the monitoring of liver injury.

In clinical trials, meaningful elevations (i.e., more than 3 times the ULN) of AST (SGOT) (ALT was not measured in all studies) occurred in about 2% of approximately 5700 patients at some time during diclofenac sodium treatment. In a large, open, controlled trial, meaningful elevations of ALT and/or AST occurred in about 4% of 3700 patients treated for 2 to 6 months, including marked elevations (i.e., more than 8 times the ULN) in about 1% of the 3700 patients. In that open-label study, a higher incidence of borderline (less than 3 times the ULN), moderate (3 to 8 times the ULN), and marked (> 8 times the ULN) elevations of ALT or AST was observed in patients receiving diclofenac when compared to other NSAIDs. Transaminase elevations were seen more frequently in patients with osteoarthritis than in those with rheumatoid arthritis (see ADVERSE REACTIONS).

In addition to the enzyme elevations seen in clinical trials, rare cases of severe hepatic reactions, including jaundice and fatal fulminant hepatitis, have been reported.

Physicians should measure transaminases periodically in patients receiving long-term therapy with diclofenac, because severe hepatotoxicity may develop without a prodrome of distinguishing symptoms. The optimum times for making the first and subsequent transaminase measurements are not known. In the largest U.S. trial (open-label), that involved 3700 patients monitored first at 8 weeks and 1200 patients monitored again at 24 weeks, almost all meaningful elevations in transaminases were detected before patients became symptomatic. In 42 of the 51 patients in all trials who developed marked transaminase elevations, abnormal tests occurred during the first 2 months of therapy with diclofenac. Based on this experience, if diclofenac is used chronically, the first transaminase measurement should be made no later than 8 weeks after the start of diclofenac treatment. As with other NSAIDs, if abnormal liver tests persist or worsen, if clinical signs and/or symptoms consistent with liver disease develop, or if systemic manifestations occur (e.g., eosinophilia, rash, etc.), diclofenac should be discontinued.

To minimize the possibility that hepatic injury will become severe between transaminase measurements, physicians should inform patients of the warning signs and symptoms of hepatotoxicity (e.g., nausea, fatigue, lethargy, pruritus, jaundice, right upper quadrant tenderness and “flu-like” symptoms), and the appropriate action patients should take if these signs and symptoms appear.

PRECAUTIONS

General

Allergic Reactions:

As with other NSAIDs, allergic reactions including anaphylaxis, have been reported with diclofenac. Specific allergic manifestations consisting of swelling of eyelids, lips, pharynx and larynx, urticaria, asthma, and bronchospasm, sometimes with a concomitant fall in blood pressure (severe at times) have been observed in clinical trials and/or the marketing experience with diclofenac. Anaphylaxis has rarely been reported from foreign sources; in U.S. clinical trials with diclofenac in over 6000 patients, 1 case of anaphylaxis was reported. In controlled clinical trials, allergic reactions have been observed at an incidence of 0.5%. These reactions can occur without prior exposure to the drug.

Fluid retention and edema have been observed in some patients taking diclofenac. Therefore, as with other NSAIDs, diclofenac should be used with caution in patients with a history of cardiac decompensation, hypertension, or other conditions predisposing to fluid retention.

Renal Effects:

As a class, NSAIDs have been associated with renal papillary necrosis and other abnormal renal pathology in long-term administration to animals. In oral diclofenac studies in animals, some evidence of renal toxicity was noted. Isolated incidents of papillary necrosis were observed in a few animals at high doses (20 to 120 mg/kg) in several baboon subacute studies. In patients treated with diclofenac, rare cases of interstitial nephritis and papillary necrosis have been reported (see ADVERSE REACTIONS).

A second form of renal toxicity generally associated with NSAIDs, is seen in patients with conditions leading to a reduction in renal blood flow or blood volume, where renal prostaglandins have a supportive role in the maintenance of renal perfusion. In these patients, administration of a NSAID results in a dose-dependent decrease in prostaglandin synthesis and, secondarily, in a reduction of renal blood flow, which may precipitate overt renal failure. Patients at greatest risk of this reaction are those with impaired renal function, heart failure, liver dysfunction, those taking diuretics, and the elderly. Discontinuation of NSAID therapy is typically followed by recovery to the pretreatment state.

Cases of significant renal failure in patients receiving diclofenac have been reported from marketing experience, but were not observed in over 4000 patients in clinical trials during which serum creatinine and BUN values were followed serially. There were only 11 patients (0.3%) whose serum creatinine and concurrent serum BUN values were greater than 2.0 mg/dL and 40 mg/dL, respectively, while on diclofenac (mean rise in the 11 patients: creatinine 2.3 mg/dL and BUN 28.4 mg/dL).

Since diclofenac metabolites are eliminated primarily by the kidneys, patients with significantly impaired renal function should be more closely monitored than subjects with normal renal function.

Porphyria:

The use of diclofenac in patients with hepatic porphyria should be avoided. To date, one patient has been described in whom diclofenac probably triggered a clinical attack of porphyria. The postulated mechanism. demonstrated in rats, for causing such attacks by diclofenac, as well as some other NSAIDs, is through stimulation of the porphyrin precursor deltaaminolevulinic acid (ALA).

Information for Patients

Diclofenac, like other drugs of its class, is not free of side effects. The side effects of these drugs can cause discomfort and, rarely, there are more serious side effects, such as gastrointestinal bleeding and, more rarely, liver toxicity (see WARNINGS: Hepatic Effects), which may result in hospitalization and even fatal outcomes.

NSAIDs are often essential agents in the management of arthritis and have a major role in the management of pain but they also may be commonly employed for conditions that are less serious.

Physicians may wish to discuss with their patients the potential risks (see WARNINGS, PRECAUTIONS, and ADVERSE REACTIONS) and likely benefits of NSAID treatment, particularly when the drugs are used for less serious conditions where treatment without NSAIDs may represent an acceptable alternative to both the patient and physician.

Laboratory Tests

Because serious G.I. tract ulceration and bleeding can occur without warning symptoms, physicians should follow chronically treated patients for the signs and symptoms of ulceration and bleeding and should inform them of the importance of this follow-up (see WARNINGS: Risk of G.I. Ulcerations, Bleeding, and Perforation with NSAID Therapy). If diclofenac is used chronically, patients should also be instructed to report any signs and symptoms that might be due to hepatotoxicity of diclofenac; these symptoms may be evident between visits when periodic liver laboratory tests are performed (see WARNINGS: Hepatic Effects).

Drug Interactions

Aspirin:

Concomitant administration of diclofenac and aspirin is not recommended because diclofenac is displaced from its binding sites during the concomitant administration of aspirin, resulting in lower plasma concentrations, peak plasma levels, and AUC values.

Anticoagulants:

While studies have not shown diclofenac to interact with anti-coagulants of the warfarin type, caution should be exercised, nonetheless, since interactions have been seen with other NSAIDs. Because prostaglandins play an important role in hemostasis, and NSAIDs affect platelet function as well, concurrent therapy with all NSAIDs, including diclofenac, and warfarin requires close monitoring of patients to be certain that no change in their anticoagulant dosage is required.

Digoxon, Methotrexate, Cyclosporine:

Diclofenac, like other NSAIDs, may affect renal prostaglandins and increase the toxicity of certain drugs. Ingestion of diclofenac may increase serum concentrations of digoxin and methotrexate and increase cyclosporine's nephrotoxicity. Patients who begin taking diclofenac or who increase their diclofenac dose or any other NSAID while taking digoxin, methotrexate, or cyclosporine may develop toxicity characteristics of these drugs. They should be observed closely, particularly if renal function is impaired. In case of digoxin, serum levels should be monitored.

Lithium:

Diclofenac decreases lithium renal clearance and increases lithium plasma levels. In patients taking diclofenac and lithium concomitantly, lithium toxicity may develop.

Oral Hypoglycemics:

Diclofenac does not alter glucose metabolism in normal subjects nor does it alter the effects of oral hypoglycemic agents. There are rare reports, however, from marketing experiences of changes in effects of insulin or oral hypoglycemic agents in the presence of diclofenac that necessitated changes in the doses of such agents. Both hypo- and hyperglycemic effects have been reported. A direct causal relationship has not been established, but physicians should consider the possibility that diclofenac may alter a diabetic patient’s response to insulin or oral hypoglycemic agents.

Diuretics:

Diclofenac and other NSAIDs can inhibit the activity of diuretics. Concomitant treatment with potassium-sparing diuretics may be associated with increased serum potassium levels.

Other Drugs:

In small groups of patients (7 to 10/interaction study), the concomitant administration of azathioprine, gold, chloroquine, D-penicillamine, prednisolone, doxycycline, or digitoxin did not significantly affect the peak levels and AUC values of diclofenac.

Protein Binding

In vitro, diclofenac interferes minimally or not at all with the protein binding of salicylic acid (20% decrease in binding), tolbutamide, prednisolone (10% decrease in binding), or warfarin. Benzylpenicillin, ampicillin, oxacillin, chlortetracycline, doxycycline, cephalothin, erythromycin, and sulfamethoxazole have no influence in vitro on the protein binding of diclofenac in human serum.

Drug/Laboratory Test Interactions

Effect on Blood Coagulation:

Diclofenac increases platelet aggregation time but does not affect bleeding time, plasma thrombin clotting time, plasma fibrinogen, or factors V and VII to XII. Statistically significant changes in prothrombin and partial thromboplastin times have been reported in normal volunteers. The mean changes were observed to be less than 1 second in both instances, however, and are unlikely to be clinically important. Diclofenac is a prostaglandin synthetase inhibitor, however, and all drugs that inhibit prostaglandin synthesis interfere with platelet function to some degree; therefore, patients who may be adversely affected by such an action should be carefully observed.

Carcinogenesis, Mutagenesis, Impairment of Fertility

Long-term carcinogenicity studies in rats given diclofenac sodium up to 2 mg/kg/day (12 mg/m^2/day, approximately the human dose) have revealed no significant increases in tumor incidence. There was a slight increase in benign mammary fibroadenomas in mid-dose-treated (0.5 mg/kg/day or 3 mg/m^2/day) female rats (high-dose females had excessive mortality), but the increase was not significant for this common rat tumor. A two-year carcinogenicity study conducted in mice employing diclofenac sodium at doses up to 0.3 mg/kg/day (0.9 mg/m^2/day) in males and 1 mg/kg/day (3 mg/m^2/day) in females did not reveal any oncogenic potential. Diclofenac sodium did not show mutagenic activity in in vitro point mutation assays in mammalian (mouse lymphoma) and microbial (yeast, Ames) test systems, and was nonmutagenic in several mammalian in vitro and in vivo tests, including dominant lethal and male germinal epithelial chromosomal studies in mice, and nucleus anomaly and chromosomal aberration studies in Chinese hamsters. Diclofenac sodium administered to male and female rats at 4 mg/kg/day did not affect fertility.

Teratogenic Effects

There are no adequate and well-controlled studies in pregnant women. Diclofenac should be used during pregnancy only if the benefits to the mother justify the potential risk to the fetus.

Pregnancy Category B:

Reproduction studies have been performed in mice given diclofenac sodium (up to 20 mg/kg/day or 60 mg/m^2/day) and in rats and rabbits given diclofenac sodium (up to 10 mg/kg/day or 60 mg/m^2/day for rats, and 80 mg/m^2/day for rabbits), and have revealed no evidence of teratogenicity despite the induction of maternal toxicity and fetal toxicity. In rats, maternally toxic doses were associated with dystocia, prolonged gestation, reduced fetal weights and growth, and reduced fetal survival. Diclofenac has been shown to cross the placental barrier in mice and rats.

Labor and Delivery

The effects of diclofenac on labor and delivery in pregnant women are unknown. Because of the known effects of postaglandin-inhibiting drugs on the fetal cardiovascular system (closure of ductus arteriosus), use of diclofenac during late pregnancy should be avoided and, as with other nonsteriodal anti-inflammatory drugs, it is possible that diclofenac may inhibit uterine contraction.

Nursing Mothers

Diclofenac has been found in the milk of nursing mothers. As with other drugs that are excreted in milk, diclofenac is not recommended for use in nursing women.

Pediatric Use

Safety and effectiveness of diclofenac in pediatric patients have not been established.

Geriatic Use

Of the more than 6000 patients treated with diclofenac in U.S. trials, 31% were older than 65 years of age. No overall difference was observed between efficacy, adverse event or pharmacokinetic profiles of older and younger patients. As with any NSAID, the elderly are likely to tolerate adverse reactions less well than younger patients.

ADVERSE REACTIONS

Adverse reaction information is derived from blinded, controlled and open-label clinical trials as well as worldwide marketing experience. In the description below, rates of more common events represent clinical study results; rarer events are derived principally from marketing experience and publications, and accurate rate estimates are generally not possible.

The incidence of common adverse reactions (greater than 1%) is based upon controlled clinical trials in 1543 patients treated up to 13 weeks with diclofenac sodium delayed-release tablets. By far the most common adverse effects were gastrointestinal symptoms, most of them minor, occurring in about 20%, and leading to discontinuation in about 3%, of patients. Peptic ulcer or G.I. bleeding occurred in clinical trials in 0.6% (95%-confidence interval: 0.2% to 1%) of approximately 1800 patients during their first 3 months of diclofenac treatment and 1.6% (95%-confidence interval: 0.8% to 2.4%) of approximately 800 patients followed for 1 year.

Gastrointestinal symptoms were followed in frequency by central nervous system side effects such as headache (7%) and dizziness (3%).

Meaningful (exceeding 3 times the Upper Limit of Normal) elevations of ALT (SGPT) or AST (SGOT) occurred at an overall rate of approximately 2% during the first 2 months of diclofenac sodium treatment. Unlike aspirin-related elevations, which occur more frequently in patients with rheumatoid arthritis, these elevations were more frequently observed in patients with osteoarthritis (2.6%) than in patients with rheumatoid arthritis (0.7%). Marked elevations (exceeding 8 times the ULN) were seen in 1% of patients treated for 2 to 6 months (see WARNINGS: Hepatic Effects).

The following adverse reactions were reported in patients treated with diclofenac:

Incidence Greater Than 1%–Causal Relationship Probable

(All derived from clinical trials)

Body as a Whole:

Abdominal pain or cramps*, headache*, fluid retention, abdominal distention.

Digestive:

Diarrhea*, indigestion*, nausea*, constipation*, flatulence, liver test abnormalities*, PUB, i.e., peptic ulcer, with or without bleeding and/or perforation, or bleeding without ulcer (see above and also WARNINGS).

Nervous System:

Dizziness.

Skin and Appendages:

Rash, pruritus.

Special Senses:

Tinnitus.

*Incidence, 3% to 9% (incidence of unmarked reactions is 1 to 3%)

Incidence Less Than 1% - Causal Relationship Probable

The following reactions have been reported in patients taking diclofenac under circumstances that do not permit a clear attribution of the reaction to diclofenac. These reactions are being included as alerting information for physicians. Adverse reactions reported only in worldwide marketing experience or in the literature, not seen in clinical trials, are considered rare and are italicized.

Body as a Whole:

Malaise, swelling of lips and tongue, photosensitivity, anaphylaxis, anaphylactoid reactions.

Cardiovascular:

Hypertension, congestive heart failure.

Digestive:

Vomiting, jaundice, melena, aphthous stomatitis, dry mouth and mucous membranes, bloody diarrhea, hepatitis, hepatic necrosis, appetite change, pancreatitis with or without concomitant hepatitis, colitis.

Hemic and Lymphatic:

Hemoglobin decrease, leukopenia, thrombocytopenia, hemolytic anemia, aplastic anemia, agranulocytosis, purpura, allergic purpura.

Metabolic and Nutritional Disorders:

Azotemia.

Nervous System:

Insomnia, drowsiness, depression, diplopia, anxiety, irritability, aseptic meningitis.

Respiratory:

Epistaxis, asthma, laryngeal edema.

Skin and Appendages:

Alopecia, urticaria, eczema, dermatitis, bullous eruption, erythema multiforme major, angioedema, Stevens-Johnson syndrome.

Special Senses:

Blurred vision, taste disorder, reversible hearing loss, scotoma.

Urogenital:

Nephrotic syndrome, proteinuria, oliguria, interstitial nephritis, papillary necrosis, acute renal failure.

Incidence Less Than 1% - Causal Relationship Unknown

(Adverse reactions reported only in worldwide marketing experience or in the literature, not seen in clinical trials, are considered rare and are italicized.)

Body as a Whole:

Chest pain.

Cardiovascular:

Palpitations, flushing, tachycardia, premature ventricular contractions, myocardial infarction.

Digestive:

Esophageal lesions.

Hemic and Lymphatic:

Bruising.

Metabolic and Nutritional Disorders:

Hypoglycemia, weight loss.

Nervous System:

Paresthesia, memory disturbance, nightmares, tremor, tic, abnormal coordination, convulsions, disorientation, psychotic reaction.

Respiratory:

Dyspnea, hyperventilation, edema of pharynx.

Skin and Appendages:

Excess perspiration, exfoliative dermatitis.

Special Senses:

Vitreous floaters, night blindness, amblyopia.

Urogenital:

Urinary frequency, nocturia, hematuria, impotence, vaginal bleeding.

OVERDOSAGE

Worldwide reports on overdosage with diclofenac cover 66 cases. In approximately one-half of these reports of overdosage, concomitant medications were also taken. The highest dose of diclofenac was 5 g in a 17-year-old male who suffered loss of consciousness, increased intracranial pressure, aspiration pneumonitis, and died 2 days after overdose. The next highest doses of diclofenac were 4 g and 3.75 g. The 24-year-old female who took 4 g and the 28- and 42-year-old females, each of whom took 3.75 g, did not develop any clinically significant signs or symptoms. However, there was a report of a 17-year-old female who experienced vomiting and drowsiness after an overdose of 2.37 g of diclofenac.

Animal LD50 values show a wide range of susceptibilities to acute overdosage, with primates being more resistant to acute toxicity than rodents (LD50 in mg/kg–rats, 55; dogs, 500; monkeys, 3200).

In case of acute overdosage it is recommended that the stomach be emptied by vomiting or lavage. Forced diuresis may theoretically be beneficial because the drug is excreted in the urine. The effect of dialysis or hemoperfusion in the elimination of diclofenac (99% protein-bound, see CLINICAL PHARMACOLOGY) remains unproven. In addition to supportive measures, the use of oral activated charcoal may help to reduce the absorption of diclofenac.

DOSAGE AND ADMINISTRATION

Diclofenac sodium may be administered as 25 mg, 50 mg, or 75 mg delayed-release tablets. Regardless of the indication, the dosage of diclofenac should be individualized to the lowest effective dose to minimize adverse effects (see CLINICAL PHARMACOLOGY: Individualization of Dosage)

Osteoarthritis:

The recommended dosage is 100 to 150 mg/day in divided doses, 50 mg b.i.d. or t.i.d. or 75 mg b.i.d. Dosages above 150 mg/day have not been studied in patients with osteoarthritis.

Rheumatoid Arthritis:

The recommended dosage is 150 to 200 mg/day in divided doses, 50 mg t.i.d. or q.i.d., or 75 mg b.i.d. Dosages above 225 mg/day are not recommended in patients with rheumatoid arthritis.

Ankylosing Spondylitis:

The recommended dosage is 100 to 125 mg/day, administered as 25 mg q.i.d., with an extra 25 mg dose at bedtime if necessary. Dosages above 125 mg/day have not been studied in patients with ankylosing spondylitis.

HOW SUPPLIED

Diclofenac Sodium Delayed-Release Tablets USP

25 mg white, round, enteric-coated tablets

Tablets Identified 54 140

NDC 0054-8223-25: Unit dose, 10 tablets per strip, 10 strips per shelf pack, ten shelf packs per shipper.

NDC 0054-4223-25: Bottles of 100 tablets.

50 mg white, round, enteric-coated tablets

Tablets Identified 54 592

NDC 0054-8221-25: Unit dose, 10 tablets per strip, 10 strips per shelf pack, ten shelf packs per shipper.

NDC 0054-4221-25: Bottles of 100 tablets.

NDC 0054-4221-31: Bottles of 1000 tablets.

75 mg white, round, enteric-coated tablets

Tablets Identiied 54 839

NDC 0054-8222-25: Unit dose, 10 tablets per strip, 10 strips per shelf pack, ten shelf packs per shipper.

NDC 0054-4222-25: Bottles of 100 tablets.

NDC 0054-4222-31: Bottles of 1000 tablets.

Do not store above 30°C (86°F).

Protect from moisture.

Dispense in a tight, light-resistant container as defined in the USP/NF.

4048700//03

© RLI, 2005